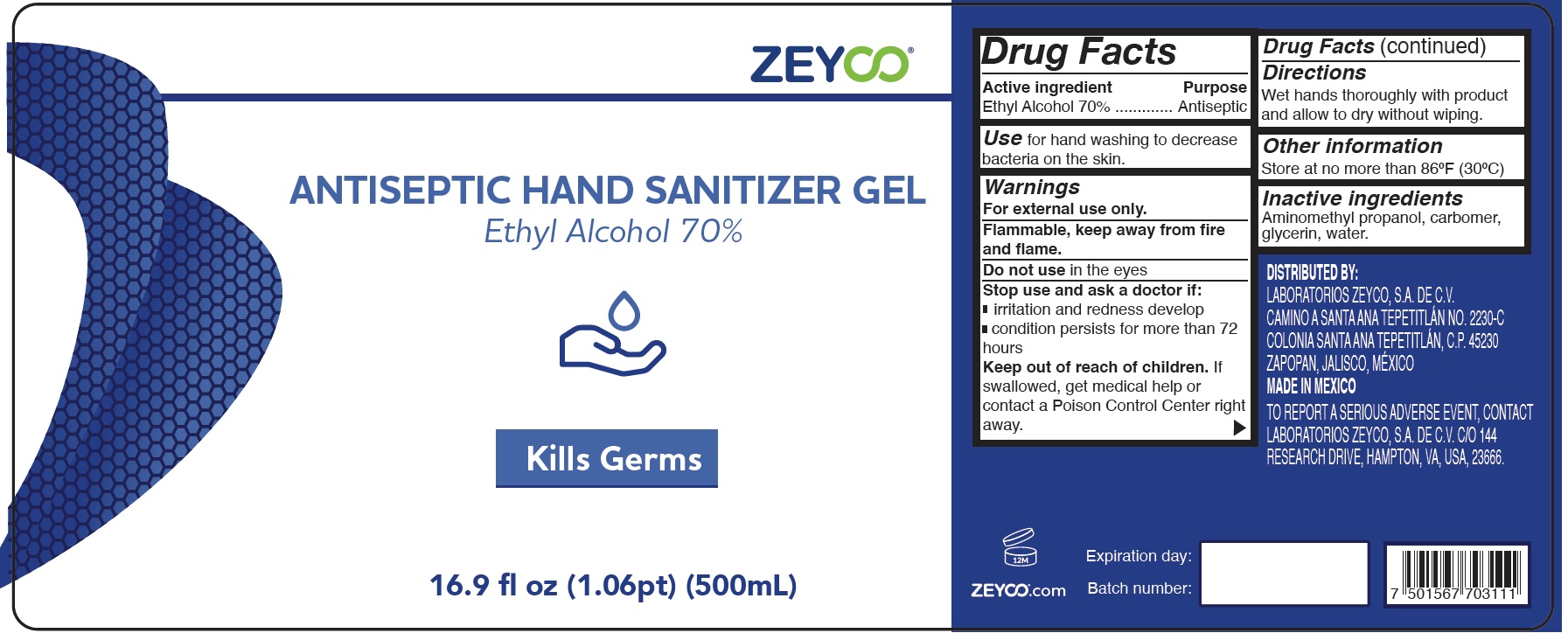 DRUG LABEL: Zeyco Hand Sanitizer
NDC: 63710-003 | Form: GEL
Manufacturer: Laboratorios Zeyco, S.A. de C.V.
Category: otc | Type: HUMAN OTC DRUG LABEL
Date: 20231026

ACTIVE INGREDIENTS: ALCOHOL 0.7 mL/1 mL
INACTIVE INGREDIENTS: AMINOMETHYLPROPANOL; CARBOMER HOMOPOLYMER, UNSPECIFIED TYPE; GLYCERIN; WATER

Zeyco Hand Sanitizer Gel

Active ingredient

Ethyl Alcohol 70%

Purpose

Antiseptic

Use

for hand washing to decrease bacteria on the skin.

Warnings

For external use only.

Flammable, keep away from fire and flame.

Do not use

in the eyes

Stop use and ask a doctor if:

- irritation and redness develop
- condition persists for more than 72 hours

Keep out of reach of children.

If swallowed, get medical help or contact a Poison Control Center right away.

Directions

Wet hands thoroughly with product and allow to dry without wiping.

Other information

Store at no more than 86ºF (30ºC)

Inactive ingredients

Aminomethyl propanol, carbomer, glycerin, water.